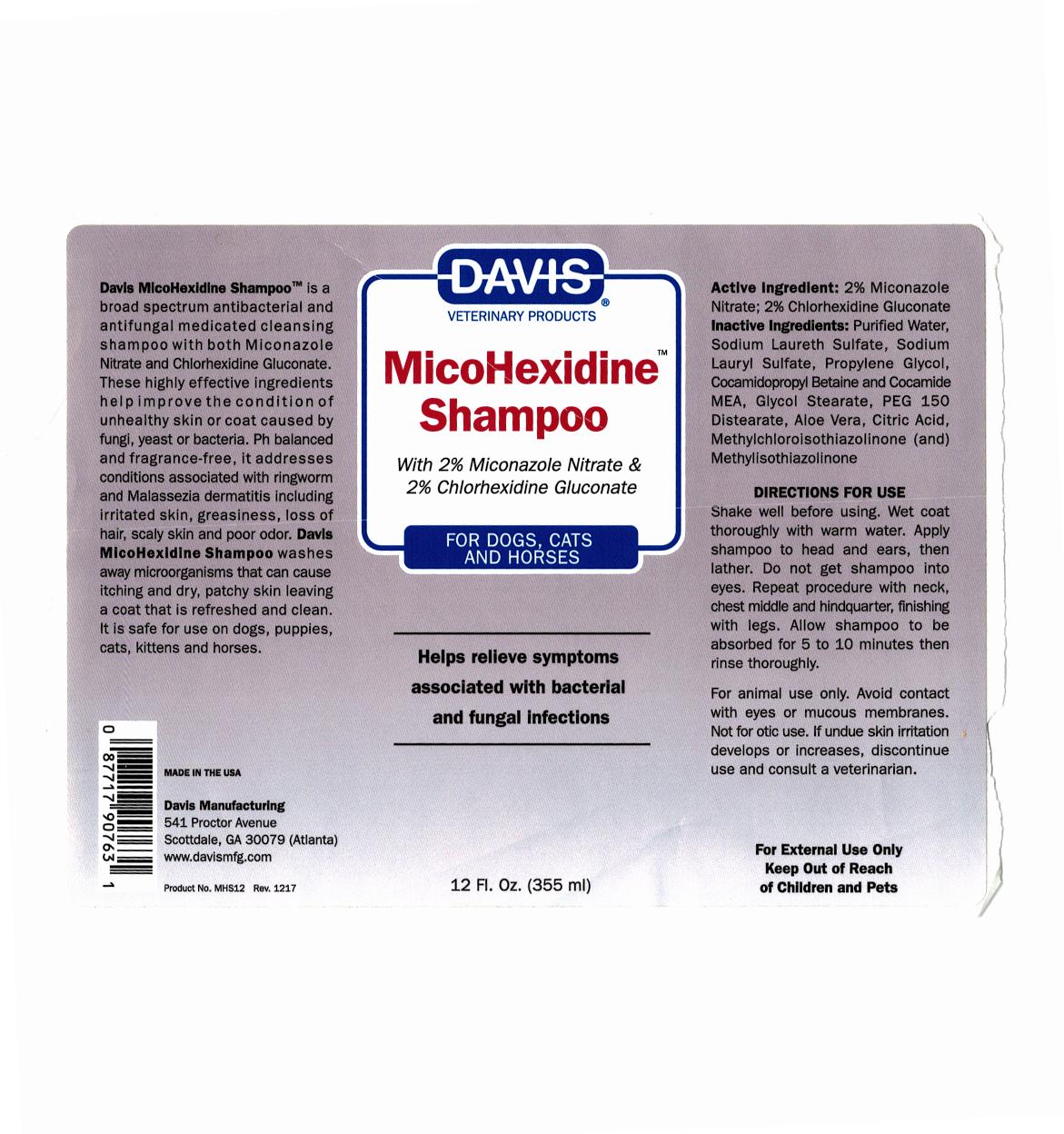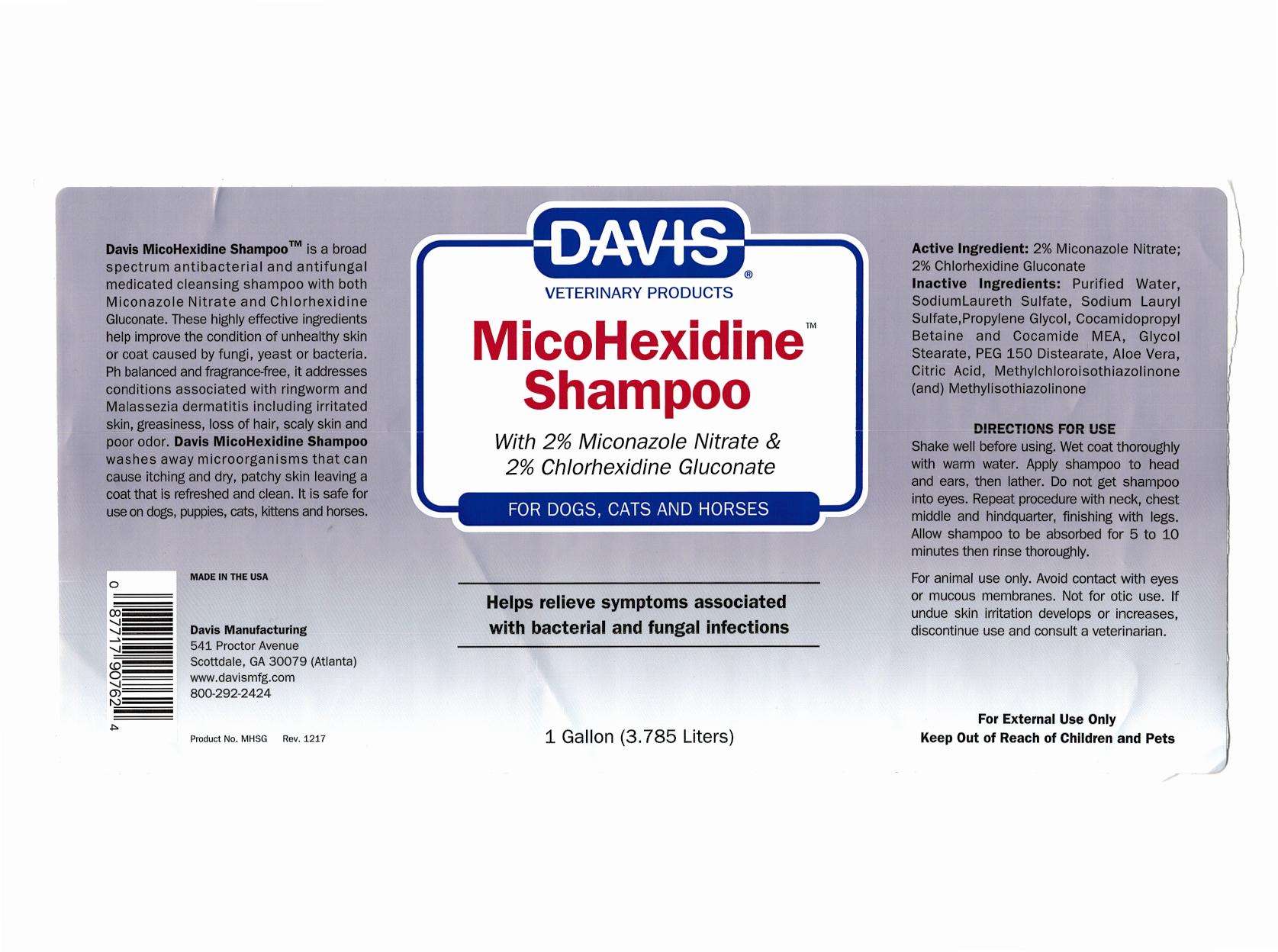 DRUG LABEL: Davis MicoHexidine
NDC: 62570-120 | Form: SHAMPOO
Manufacturer: DAVIS MANUFACTURING AND PACKAGING INC
Category: animal | Type: OTC ANIMAL DRUG LABEL
Date: 20180626

ACTIVE INGREDIENTS: MICONAZOLE NITRATE 20 mg/1 g; CHLORHEXIDINE GLUCONATE 20 g/1 g
INACTIVE INGREDIENTS: WATER; SODIUM LAURETH SULFATE; SODIUM LAURYL SULFATE; PROPYLENE GLYCOL; COCAMIDOPROPYL BETAINE; SODIUM; COCO MONOETHANOLAMIDE; GLYCOL STEARATE; GLYCERYL 1,3-DISTEARATE; ALOE VERA LEAF; ANHYDROUS CITRIC ACID; METHYLCHLOROISOTHIAZOLINONE/METHYLISOTHIAZOLINONE MIXTURE

Davis MicoHexidineTM Shampoo

DESCRIPTION

Davis MicoHexidine ShampooTM is a broad spectrum antibacterial and antifungal medicated cleansing shampoo with both Miconazole Nitrate and Chlorhexidine Gluconate. These highly effective ingredients help improve the condition of the unhealthy skin or coat caused by fungi, yeast or bacteria. pH balanced and fragrance-free, it addresses conditions associated with ringworm and Malassezia dermititis including irritated skin, greasiness, loss of hair, scaly skin and poor odor. Davis MicoHexidine Shampoo washes away microorganisims that can cause itching and dry, patchy skin leaving a coat that is refreshed and clean. It is safe for use on dogs, puppies, cats, kittens, and horses.

MADE IN THE USA

Davis Manufacturing

541 Proctor Avenue

Scottdale, GA 30079 (Atlanta)

www.davismfg.com

Active Ingredient: 2% Miconazole Nitrate; 2% Chlorhexidine Gluconate

INACTIVE INGREDIENT

Inactive Ingredients: Purified Water, Sodium Laureth Sulfate, Sodium Lauryl Sulfate, Propylene Glycol, Cocamidopropyl Betaine and Cocamide MEA, Glycol Stearate, PEG 150 Distearate, Aloe Vera, Citric Acid, Methylchloroisothiazolinone (and) Methylisothiazolinone

Directions For Use

Shake well before using. Wet coat thoroughly with warm water. Apply shampoo to head and ears, then lather. Do not get shampoo into eyes. Repeat procedure with neck, chest middle and hindquarter, finish with legs. Allow shampoo to be absorbed for 5 to 10 minutes then rinse thoroughly.

WARNINGS AND PRECAUTIONS

For animal use only. Avoid contact with eyes or mucous membranes. Not for otic use. If undue skin irritation develops or increases, discontinue use and consult a veterinarian.

KEEP OUT OF REACH OF CHILDREN

For External Use Only.

Keep Out of Reach of Children and Pets

Principal Display Panel 355 ml

Davis Veterinary Products

MicoHexidineTM Shampoo

with 2% Miconazole Nitrate & 2% Chlorhexidine Gluconate

FOR DOGS, CATS AND HORSES

Helps relieve symptoms associated with bacterial and fingal infections

12 Fl. Oz. (355 ml)

PACKAGE LABEL

Davis Veterinary Products

MicoHexidineTM Shampoo

with 2% Miconazole Nitrate & 2% Chlorhexidine Gluconate

FOR DOGS, CATS AND HORSES

Helps relieve symptoms associated with bacterial and fingal infections

1 Gallon (3.785 Liters)